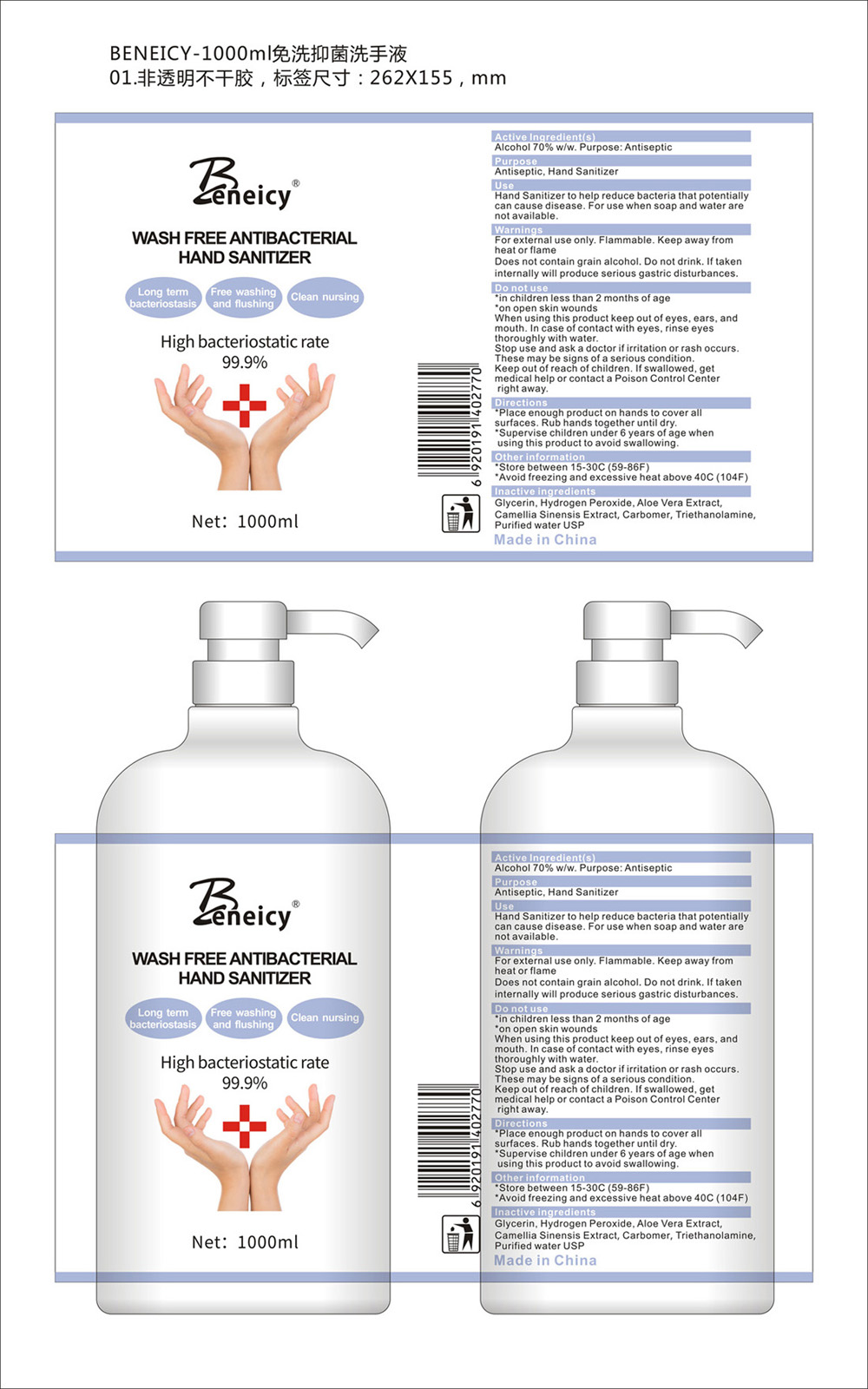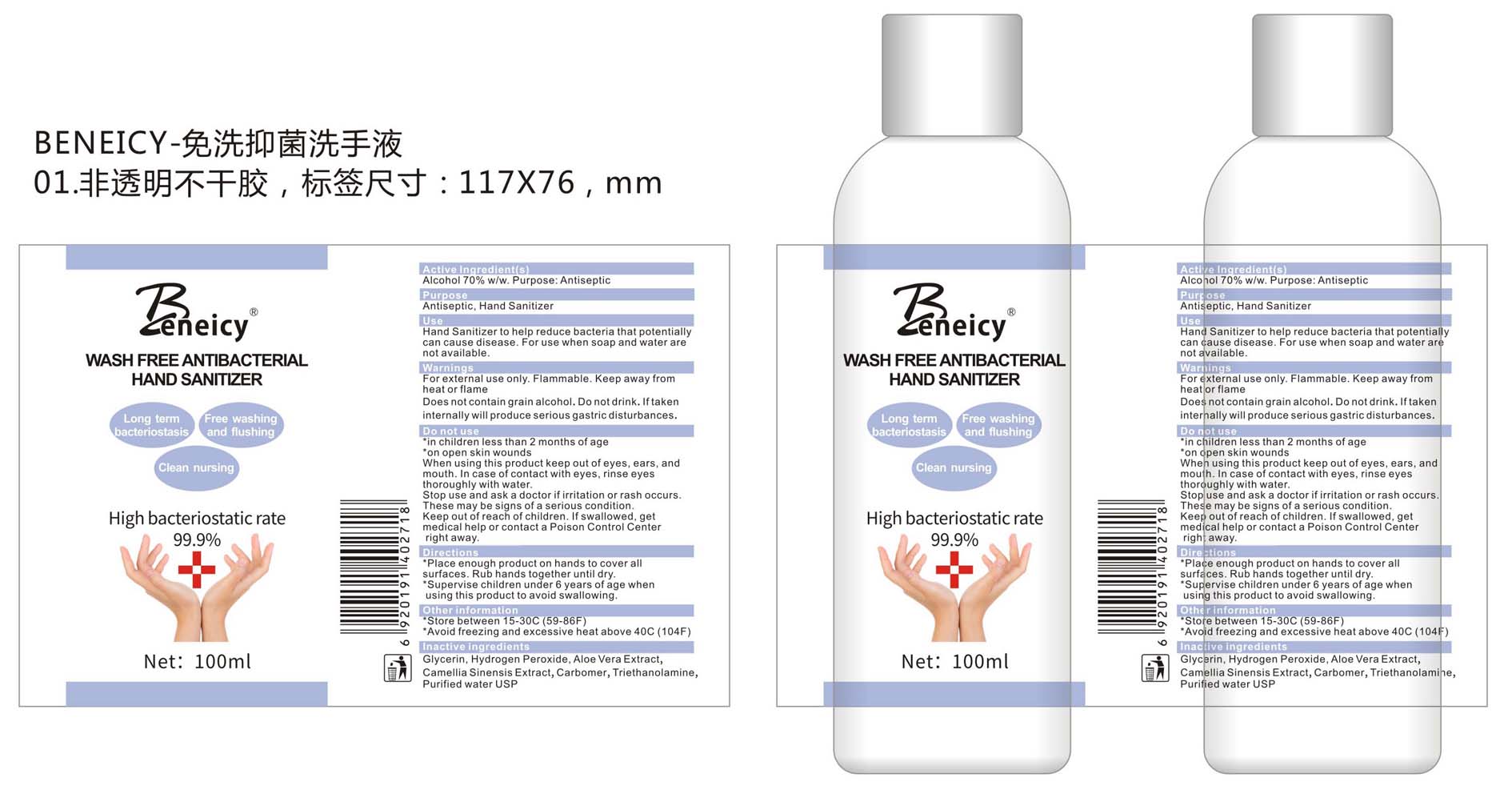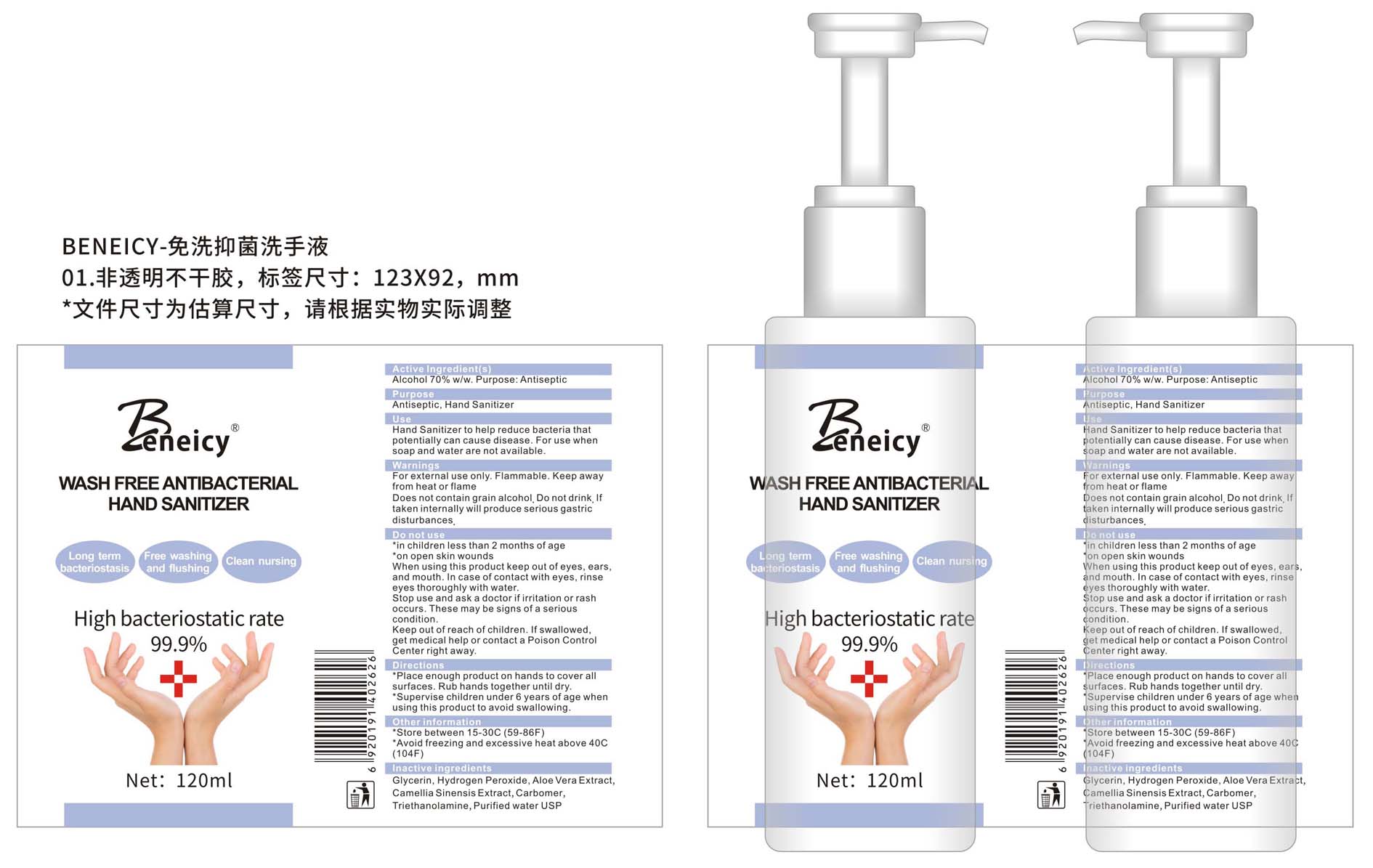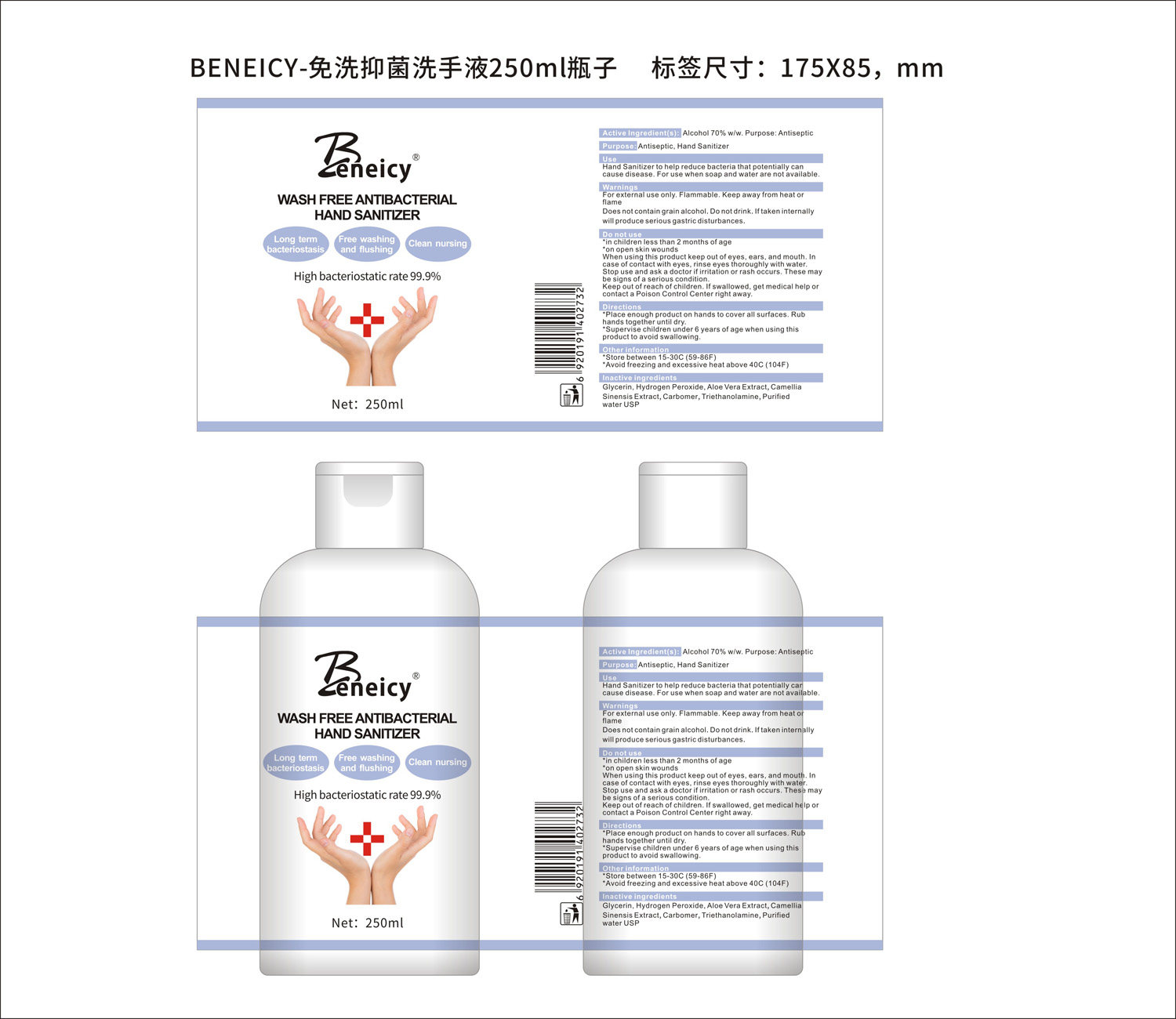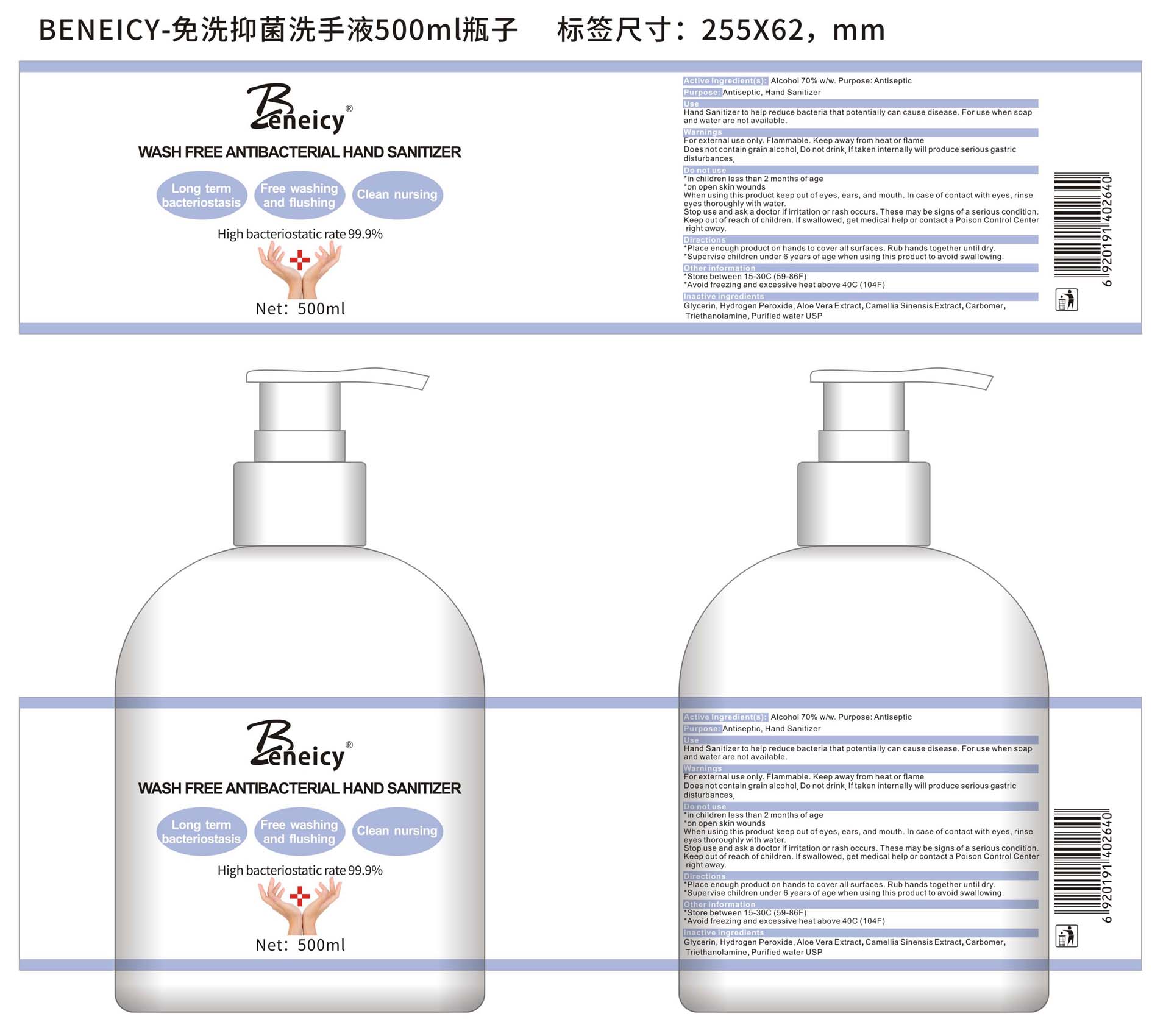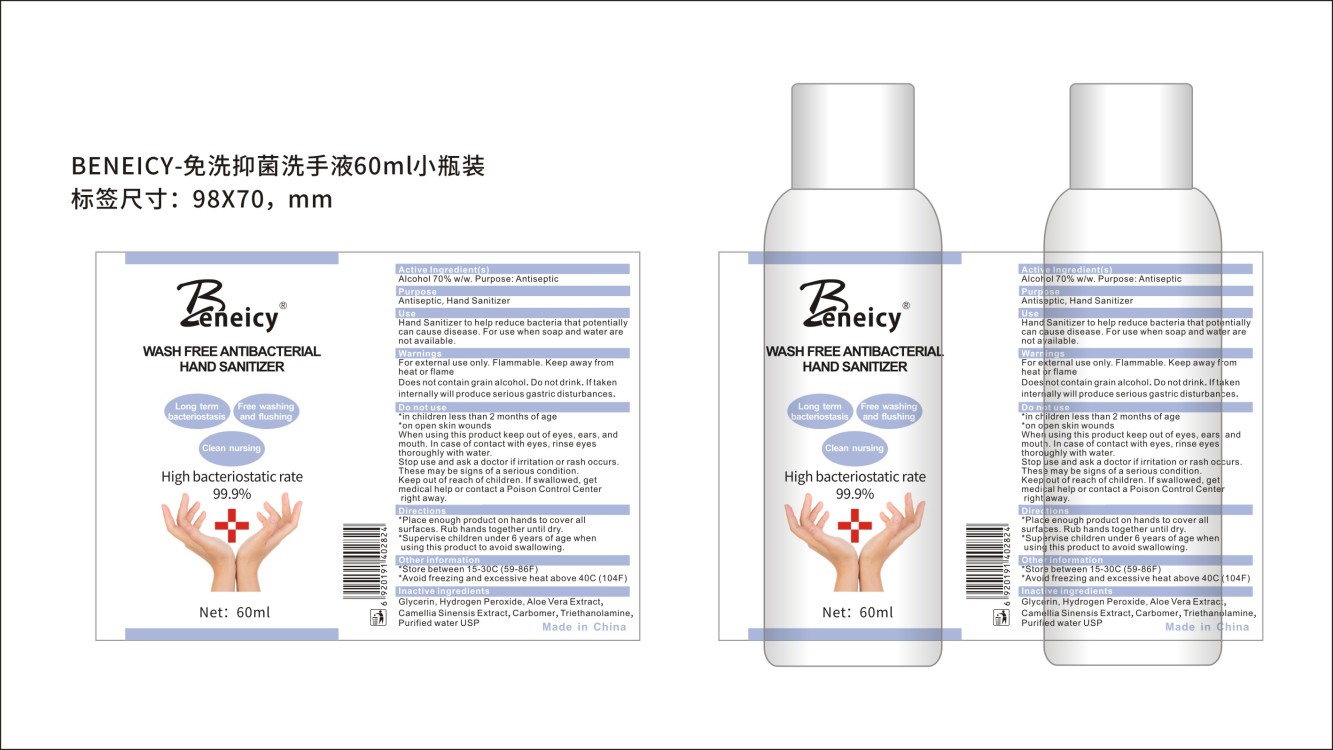 DRUG LABEL: BENEICY WASH FREE ANTIBACTERIAL HAND SANITIZER
NDC: 75761-001 | Form: GEL
Manufacturer: Guangzhou ocean cosmetic co.,ltd.
Category: otc | Type: HUMAN OTC DRUG LABEL
Date: 20200421

ACTIVE INGREDIENTS: ALCOHOL 70 L/100 L
INACTIVE INGREDIENTS: GLYCERIN 1 L/100 L; ALOE VERA LEAF 1 L/100 L; WATER 26.3 L/100 L; CARBOMER COPOLYMER TYPE A (ALLYL PENTAERYTHRITOL CROSSLINKED) 0.25 L/100 L; TRIETHANOLAMINE LAURYL SULFATE 0.25 L/100 L; CAMELLIA SINENSIS FLOWER 1 L/100 L; PANTHENOL 0.2 L/100 L

Active Ingredient(s)

Ethyl Alcohol 70%

Purpose

Antiseptic, Hand Sanitizer

Use

Hand Sanitizer to help reduce bacteria that potentially can cause disease. For use when soap and water are not available.

Warnings

For external use only. Flammable. Keep away from heat or flame

Do not use

- in children less than 2 months of age
- on open skin wounds

When using this product keep out of eyes, ears, and mouth. In case of contact with eyes, rinse eyes thoroughly with water.

Stop use and ask a doctor if irritation or rash occurs. These may be signs of a serious condition.

Keep out of reach of children. If swallowed, get medical help or contact a Poison Control Center right away.

Directions

- Place enough product on hands to cover all surfaces. Rub hands together until dry.
- Supervise children under 6 years of age when using this product to avoid swallowing.

Other information

- Store between 15-30C (59-86F)
- Avoid freezing and excessive heat above 40C (104F)

Inactive ingredients

Glycerin, Hydrogen Peroxide, Aloe Vera Extract, Camellia Sinensis Extract, Carbomer, Triethanolamine, Purified water USP